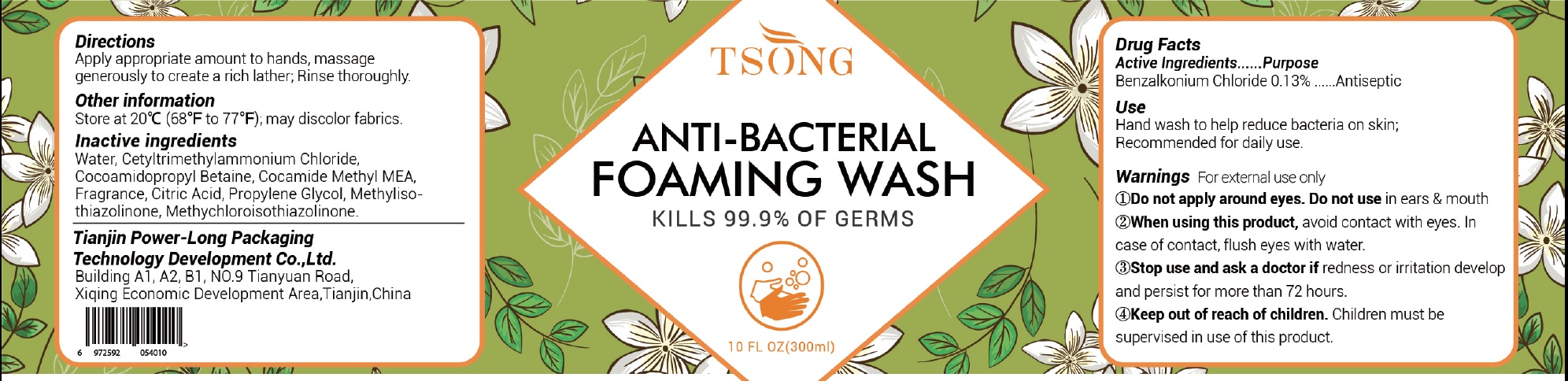 DRUG LABEL: TSONG Anti Bacterial Foaming Hand Wash
NDC: 79035-001 | Form: LIQUID
Manufacturer: Tianjin Power-Long Packaging Technology Development Co.,Ltd.
Category: otc | Type: HUMAN OTC DRUG LABEL
Date: 20231207

ACTIVE INGREDIENTS: BENZALKONIUM CHLORIDE 1.3 mg/1 mL
INACTIVE INGREDIENTS: WATER; CETRIMONIUM CHLORIDE; COCAMIDOPROPYL BETAINE; COCOYL METHYL MONOETHANOLAMINE; SODIUM CHLORIDE; CITRIC ACID MONOHYDRATE; METHYLISOTHIAZOLINONE; METHYLCHLOROISOTHIAZOLINONE

TSONG Anti-Bacterial Foaming Hand Wash

Active Ingredients

Benzalkonium Chloride 0.13%

Purpose

Antiseptic

Use

Hand wash to help reduce bacteria on skin; Recommended for daily use.

Warnings

For external use only

Do not apply around eyes.

Do not use

in ears & mouth

When using this product,

avoid contact with eyes. In case of contact, flush eyes with water.

Stop use and ask a doctor if

redness or irritation develop and persist for more than 72 hours.

Keep out of reach of children.

Children must be supervised in use of this product.

Directions

Apply appropriate amount to hands, massage generously to create a rich lather; Rinse thoroughly.

Other information

Store at 20°C (68°F to 77°F), may discolor fabrics.

Inactive ingredients

Water, Cetyltrimethylammonium Chloride, Cocoamidopropyl Betaine, Cocamide Methyl MEA, Sodium Chloride, Fragrance, Citric Acid, Methylisothiazolinone, Methylchloroisothiazolinone.